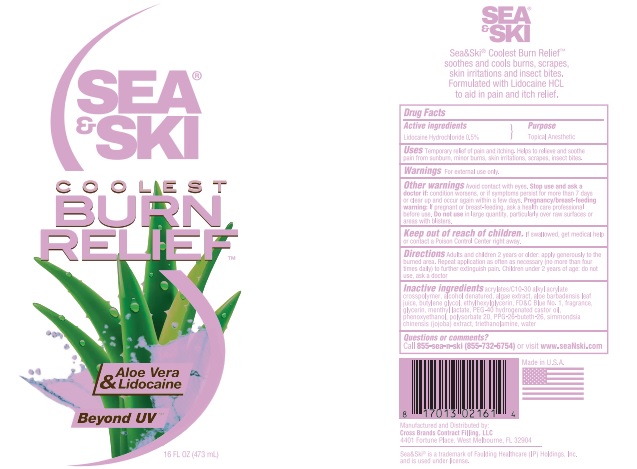 DRUG LABEL: Burn Relief Gel
NDC: 73440-2161 | Form: GEL
Manufacturer: Cross Brands Contract Filling
Category: otc | Type: HUMAN OTC DRUG LABEL
Date: 20210219

ACTIVE INGREDIENTS: LIDOCAINE HYDROCHLORIDE 2.4123 g/482.46 g
INACTIVE INGREDIENTS: WATER 436.1 g/482.46 g

Coolest Burn Relief 16oz

Active Ingredients

Lidocaine Hydrochloride 0.5%

Purpose

Topical Anesthetic

Uses

Temporary relief of pain and itching. Helps to relieve and soothe pain from sunburn, minor burns, skin irritations, scrapes, insect bites.

Warnings

For external use only

Other Warnings

Avoid Contact with eyes.

Stop use and ask a doctor if:

condition worsens, or if symptoms persist for more than 7 days or clear up and occur again within a few days.

Pregnancy/breast-feeding warning

If pregnant or breast-feeding, as a health care professional before use.

Do not use

in large quantity, particularly over raw surfaces or areas with blisters.

Keep out of reach of children.

If swallowed, get medical help or contact a Poison Control Center right away.

Directions

Adults and children 2 years or older: apply generously to the burned area. Repeat application as often as necessary (no more than four times daily) to further extinguish pain. Children under 2 years of age: do not use, ask a doctor

Inactive ingredients

acrylates/C1030 alkyl acrylate crosspolymer, alcohol denatured, algae extract, aloe barbadensis leaf juice, butylene glycol, ehtylhexylglycerin, FD&C Blue No. 1, fragrance, glycerin, menthyl lactate, PEG-40 hydrogenated castor oil, phenoxyethanol, polysorbate 20, PPG-26-butheth-26, simmondsia chinensis (jojoba) extract, triethanolamine, water.

Questions or comments?

Call 855-sea-n-ski (855-732-6754) or visit www.seaNski.com